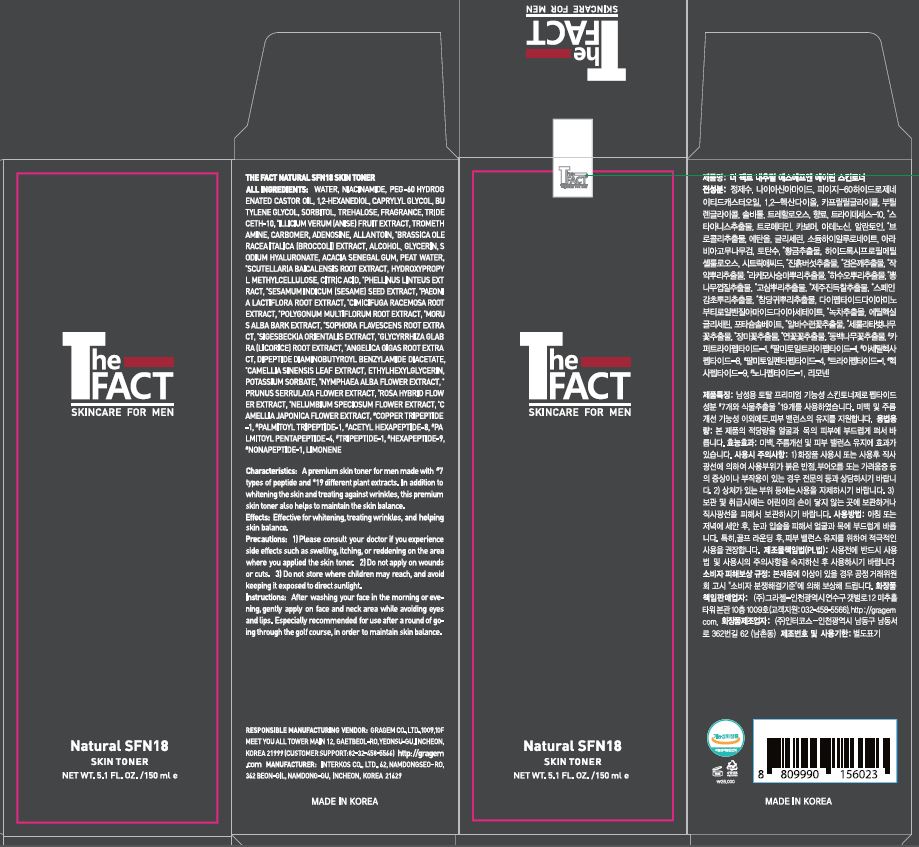 DRUG LABEL: The Fact Natural SFN 18 Skin Toner
NDC: 77049-0012 | Form: LIQUID
Manufacturer: Interkos Co.,Ltd.
Category: otc | Type: HUMAN OTC DRUG LABEL
Date: 20220120

ACTIVE INGREDIENTS: NIACINAMIDE 2 g/100 mL; ADENOSINE 0.04 g/100 mL
INACTIVE INGREDIENTS: BUTYLENE GLYCOL; GLYCERIN; WATER

Drug Facts

ACTIVE INGREDIENT

niacinamide, adenosine

INACTIVE INGREDIENT

water, carbomer, sorbitol, allantoin, glycerin, etc

PURPOSE

for skin protectant

KEEP OUT OF REACH OF THE CHILDREN

INDICATIONS AND USAGE

Take an appropriate amount on your hands and apply it to your face.

WARNINGS

1) Please consult your doctor if you experience side effects such as swelling, itching, or reddening on the area where you applied this product

2) Do not apply on wounds or cuts. 3) Do not store where children may reach, and avoid keeping it exposed to direct sunlight.

DOSAGE AND ADMINISTRATION

external use only